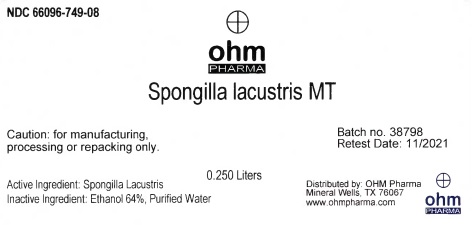 DRUG LABEL: Spongilla lacustris MT
NDC: 66096-749 | Form: TINCTURE
Manufacturer: OHM PHARMA INC.
Category: homeopathic | Type: HUMAN PRESCRIPTION DRUG LABEL
Date: 20211229

ACTIVE INGREDIENTS: SPONGILLA LACUSTRIS 1 [hp_X]/0.25 L
INACTIVE INGREDIENTS: WATER; ALCOHOL

Spongilla lacustris MT

Active Ingredient: Spongilla Lacustris

WARNINGS

Caution: for manufacturing,

processing or repacking only.

Inactive Ingredient: Ethanol 64%, Purified Water

QUESTIONS

Distributed by: OHM Pharma

Mineral Wells, TX 76067

www.ohmpharma.com

PACKAGE LABEL

NDC 66096-749-08

ohm

PHARMA

Spongilla lacustris MT

0.250

Caution: for manufacturing,

processing or repacking only.

Batch no. 38798

Retest Date: 11/2021

Active Ingredient: Spongilla Lacustris

Inactive Ingredient: Ethanol 64%, Purified Water

Distributed by: OHM Pharma

Mineral Wells, TX 76067

www.ohmpharma.com